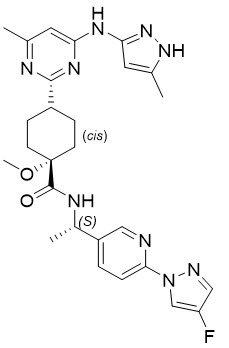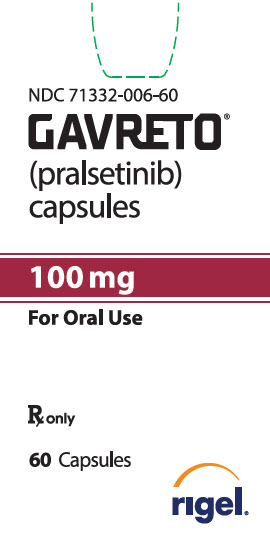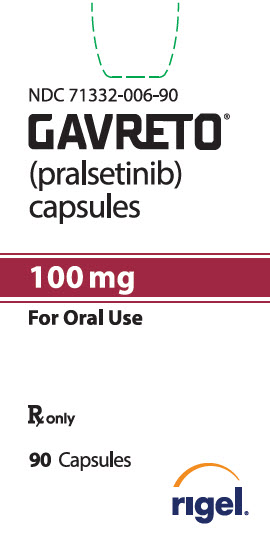 DRUG LABEL: Gavreto
NDC: 71332-006 | Form: CAPSULE
Manufacturer: Rigel Pharmaceuticals, Inc.
Category: prescription | Type: HUMAN PRESCRIPTION DRUG LABEL
Date: 20251230

ACTIVE INGREDIENTS: PRALSETINIB 100 mg/1 1
INACTIVE INGREDIENTS: HYDROXYPROPYL CELLULOSE, UNSPECIFIED; SODIUM BICARBONATE; ANHYDROUS CITRIC ACID; MAGNESIUM STEARATE

HIGHLIGHTS OF PRESCRIBING INFORMATION

These highlights do not include all the information needed to use GAVRETO safely and effectively. See full prescribing information for GAVRETO.
GAVRETO® (pralsetinib) capsules, for oral use
Initial U.S. Approval: 2020

WARNING: SERIOUS INFECTIONS, INCLUDING OPPORTUNISTIC INFECTIONS

See full prescribing information for complete boxed warning.

GAVRETO may increase the risk for serious infections, including bacterial, fungal, viral and opportunistic infections, which can lead to hospitalization or death. Withhold, reduce the dose or permanently discontinue GAVRETO based on severity. (2.3, 5.1)

RECENT MAJOR CHANGES

Boxed Warning | 12/2025
Warning and Precautions - (5.1) | 12/2025
Warning and Precautions - (5.2) (6.1) | 2/2025

1 INDICATIONS AND USAGE

GAVRETO is a kinase inhibitor indicated for treatment of:

- Adult patients with metastatic rearranged during transfection (RET) fusion-positive non-small cell lung cancer as detected by an FDA approved test (NSCLC). (1.1)
- Adult and pediatric patients 12 years of age and older with advanced or metastatic RET fusion-positive thyroid cancer who require systemic therapy and who are radioactive iodine-refractory (if radioactive iodine is appropriate).
  This indication is approved under accelerated approval based on overall response rate and duration of response. Continued approval for this indication may be contingent upon verification and description of clinical benefit in confirmatory trial(s). (1.2)

2 DOSAGE AND ADMINISTRATION

- Select patients for treatment with GAVRETO based on the presence of a RET gene fusion. (2.1, 14)
- The recommended dosage in adults and pediatric patients 12 years and older is 400 mg orally once daily on an empty stomach (no food intake for at least 2 hours before and at least 1 hour after taking GAVRETO). (2.2)

3 DOSAGE FORMS AND STRENGTHS

Capsules: 100 mg. (3)

4 CONTRAINDICATIONS

None. (4)

5 WARNINGS AND PRECAUTIONS

- Serious Infections, Including Opportunistic Infections: Monitor for signs and symptoms of infection and treat appropriately. Withhold, reduce the dose, or permanently discontinue GAVRETO based on severity. (2.3, 5.1)
- Interstitial Lung Disease (ILD)/Pneumonitis: Withhold GAVRETO for Grade 1 or 2 reactions until resolution and then resume at a reduced dose. Permanently discontinue for recurrent ILD/pneumonitis. Permanently discontinue for Grade 3 or 4 reactions. (2.3, 5.2)
- Hypertension: Do not initiate GAVRETO in patients with uncontrolled hypertension. Optimize blood pressure (BP) prior to initiating GAVRETO. Monitor BP after 1 week, at least monthly thereafter and as clinically indicated. Withhold, reduce dose, or permanently discontinue GAVRETO based on severity. (2.3, 5.3)
- Hepatotoxicity: Monitor ALT and AST prior to initiating GAVRETO, every 2 weeks during the first 3 months, then monthly thereafter and as clinically indicated. Withhold, reduce dose, or permanently discontinue GAVRETO based on severity. (2.3, 5.4)
- Hemorrhagic Events: Permanently discontinue GAVRETO in patients with severe or life-threatening hemorrhage. (2.3, 5.5)
- Tumor Lysis Syndrome:Closely monitor patients at risk and treat as clinically indicated. (2.3, 5.6)
- Risk of Impaired Wound Healing:Withhold GAVRETO for at least 5 days prior to elective surgery. Do not administer for at least 2 weeks following major surgery and until adequate wound healing. The safety of resumption of GAVRETO after resolution of wound healing complications has not been established. (5.7)
- Embryo-Fetal Toxicity: Can cause fetal harm. Advise females of reproductive potential of the potential risk to a fetus and to use effective non-hormonal contraception. (5.8, 8.1, 8.3)

6 ADVERSE REACTIONS

- The most common adverse reactions (≥ 25%) were musculoskeletal pain, constipation, hypertension, diarrhea, fatigue, edema, pyrexia and cough.
- The most common Grade 3-4 laboratory abnormalities (≥ 2%) were decreased lymphocytes, decreased neutrophils, decreased hemoglobin, decreased phosphate, decreased leukocytes, decreased sodium, increased aspartate aminotransferase (AST), increased alanine aminotransferase (ALT), decreased calcium (corrected), decreased platelets, increased alkaline phosphatase, increased potassium, decreased potassium and increased bilirubin. (6)

To report SUSPECTED ADVERSE REACTIONS, contact Rigel Pharmaceuticals, Inc. at 1-800-983-1329 or FDA at 1-800-FDA-1088 or www.fda.gov/medwatch.

7 DRUG INTERACTIONS

- Strong or moderate CYP3A inhibitors and/or P-gp inhibitors: Avoid coadministration. If coadministration cannot be avoided, reduce the dose of GAVRETO. (2.4, 7.1, 12.3)
- Strong or moderate CYP3A inducers: Avoid coadministration. If coadministration cannot be avoided, increase the dose of GAVRETO. (2.5, 7.1, 12.3)

8 USE IN SPECIFIC POPULATIONS

- Lactation: Advise not to breastfeed. (8.2)
- Pediatric Use: Monitor open growth plates in adolescent patients. Consider interrupting or discontinuing GAVRETO if abnormalities occur. (8.4)

FULL PRESCRIBING INFORMATION

WARNING: SERIOUS INFECTIONS, INCLUDING OPPORTUNISTIC INFECTIONS

GAVRETO may increase the risk for serious infections, including bacterial, fungal, viral and opportunistic infections, which can lead to hospitalization or death. Withhold, reduce the dose or permanently discontinue GAVRETO based on severity [see Dosage and Administration (2.3), Warnings and Precautions (5.1)].

1 INDICATIONS AND USAGE

1.1 Metastatic RET Fusion-Positive Non-Small Cell Lung Cancer

GAVRETO is indicated for the treatment of adult patients with metastatic RET fusion-positive non-small cell lung cancer (NSCLC) as detected by an FDA approved test.

1.2 RET Fusion-Positive Thyroid Cancer

GAVRETO is indicated for the treatment of adult and pediatric patients 12 years of age and older with advanced or metastatic RET fusion-positive thyroid cancer who require systemic therapy and who are radioactive iodine-refractory (if radioactive iodine is appropriate).

This indication is approved under accelerated approval based on overall response rate and duration of response [see Clinical Studies (14.2)]. Continued approval for this indication may be contingent upon verification and description of clinical benefit in confirmatory trial(s).

2 DOSAGE AND ADMINISTRATION

2.1 Patient Selection

Select patients for treatment with GAVRETO based on the presence of a RET gene fusion (NSCLC or thyroid cancer) [see Clinical Studies (14)].

Information on FDA-approved tests for RET gene fusion (NSCLC) is available at http://www.fda.gov/CompanionDiagnostics.

An FDA-approved test for the detection of RET gene fusion (thyroid cancer) is not currently available.

2.2 Recommended Dosage

The recommended dosage of GAVRETO is 400 mg orally once daily on an empty stomach (no food intake for at least 2 hours before and at least 1 hour after taking GAVRETO) [see Clinical Pharmacology (12.3)] . Continue treatment until disease progression or until unacceptable toxicity.

If a dose of GAVRETO is missed, it can be taken as soon as possible on the same day. Resume the regular daily dose schedule for GAVRETO the next day.

Do not take an additional dose if vomiting occurs after GAVRETO but continue with the next dose as scheduled.

2.3 Dosage Modifications for Adverse Reactions

The recommended dose reductions and dosage modifications for adverse reactions are provided in Table 1 and Table 2.

Table 1: Recommended Dose Reductions for GAVRETO for Adverse Reactions
Dose Reduction | Recommended Dosage
First | 300 mg once daily
Second | 200 mg once daily
Third | 100 mg once daily

Permanently discontinue GAVRETO in patients who are unable to tolerate 100 mg taken orally once daily.

The recommended dosage modifications for adverse reactions are provided in Table 2.

Table 2: Recommended Dosage Modifications for GAVRETO for Adverse Reactions
Adverse Reactions | Severity [Adverse reactions graded by the National Cancer Institute Common Terminology Criteria for Adverse Events (NCI-CTCAE) version 4.03] | Dosage Modification
Serious Infections, Including Opportunistic Infections [see Warnings and Precautions (5.1)] | Grade 2 or 3 | Withhold GAVRETO until resolution. Resume at a reduced dose (Table 1).
Serious Infections, Including Opportunistic Infections [see Warnings and Precautions (5.1)] | Grade 4 | Permanently discontinue GAVRETO.
ILD/Pneumonitis [see Warnings and Precautions (5.2)] | Grade 1 or 2 | Withhold GAVRETO until resolution. Resume by reducing the dose as shown in Table 1. Permanently discontinue GAVRETO for recurrent ILD/pneumonitis.
ILD/Pneumonitis [see Warnings and Precautions (5.2)] | Grade 4 | Permanently discontinue GAVRETO.
Hypertension [see Warnings and Precautions (5.3)] | Grade 3 | Withhold GAVRETO for Grade 3 hypertension that persists despite optimal antihypertensive therapy. Resume at a reduced dose when hypertension is controlled.
Hypertension [see Warnings and Precautions (5.3)] | Grade 4 | Discontinue GAVRETO.
Hepatotoxicity [see Warnings and Precautions (5.4)] | Grade 3 or 4 | Withhold GAVRETO and monitor AST/ALT once weekly until resolution to Grade 1 or baseline. Resume at reduced dose (Table 1). For recurrent events at Grade 3 or higher, discontinue GAVRETO.
Hemorrhagic Events [see Warnings and Precautions (5.5)] | Grade 3 or 4 | Withhold GAVRETO until recovery to baseline or Grade 0 or 1. Discontinue GAVRETO for severe or life-threatening hemorrhagic events.
Other Adverse Reactions [see Adverse Reactions (6.1)] | Grade 3 or 4 | Withhold GAVRETO until improvement to ≤ Grade 2. Resume at reduced dose (Table 1). Permanently discontinue for recurrent Grade 4 adverse reactions.

2.4 Dose Modification for Use with CYP3A and/or P-glycoprotein (P-gp) Inhibitors

Avoid coadministration of GAVRETO with any of the following:

- Strong CYP3A inhibitors
- Moderate CYP3A inhibitors
- P-gp inhibitors
- Combined P-gp and strong CYP3A inhibitors
- Combined P-gp and moderate CYP3A inhibitors

If coadministration with any of the above inhibitors cannot be avoided, reduce the current dose of GAVRETO as recommended in Table 3. After the inhibitor has been discontinued for 3 to 5 elimination half-lives, resume GAVRETO at the dose taken prior to initiating the inhibitor [see Drug Interactions (7.1), Clinical Pharmacology (12.3)].

Table 3: Recommended Dosage Modifications for GAVRETO for Coadministration with CYP3A and/or P-gp Inhibitors
Current GAVRETO Dosage | Recommended GAVRETO Dosage when Coadministered with:
 | Combined P-gp and Strong CYP3A Inhibitors | - Strong CYP3A Inhibitors; - Moderate CYP3A Inhibitors; - P-gp Inhibitors; - Combined P-gp and Moderate CYP3A Inhibitors
400 mg orally once daily | 200 mg orally once daily | 300 mg orally once daily
300 mg orally once daily | 200 mg orally once daily | 200 mg orally once daily
200 mg orally once daily | 100 mg orally once daily | 100 mg orally once daily

2.5 Dose Modification for Use with CYP3A Inducers

Avoid coadministration of GAVRETO with any of the following:

- Strong CYP3A inducers
- Moderate CYP3A inducers

If coadministration with any of the above inducers cannot be avoided, increase the starting dose of GAVRETO as recommended in Table 4 starting on Day 7 of coadministration of GAVRETO with the inducer. After the inducer has been discontinued for at least 14 days, resume GAVRETO at the dose taken prior to initiating the inducer [see Drug Interactions (7.1), Clinical Pharmacology (12.3)].

Table 4: Recommended Dosage Modifications for GAVRETO for Coadministration with CYP3A Inducers
Current GAVRETO Dosage | Recommended GAVRETO Dosage when Coadministered with:
 | Strong CYP3A Inducers | Moderate CYP3A Inducers
400 mg orally once daily | 800 mg orally once daily | 600 mg orally once daily
300 mg orally once daily | 600 mg orally once daily | 500 mg orally once daily
200 mg orally once daily | 400 mg orally once daily | 300 mg orally once daily

3 DOSAGE FORMS AND STRENGTHS

Capsules: 100 mg, light blue, opaque, hard hydroxypropyl methylcellulose (HPMC) capsule printed with "BLU-667" on the capsule shell body and "100 mg" on the capsule shell cap.

4 CONTRAINDICATIONS

None.

5 WARNINGS AND PRECAUTIONS

5.1 Serious Infections, Including Opportunistic Infections

GAVRETO may increase the risk for serious infections, including fatal and opportunistic infections. In the AcceleRET-Lung trial [see Adverse Reactions (6.1)], infections occurred in 72% of patients who received GAVRETO, including 18% with Grade 3, 3.7% with Grade 4, and 7% with fatal outcomes. Among the patients who received chemotherapy/immunotherapy, infections occurred in 52%, including 10% with Grade 3. Infections in the GAVRETO arm included pneumonia, urinary tract infection, opportunistic infections (such as pneumocystis jirovecii pneumonia, and fungal infections) and others. Monitor patients for signs and symptoms of infection and treat appropriately. Withhold, reduce the dose, or permanently discontinue GAVRETO based on severity [see Dosage and Administration (2.3)].

5.2 Interstitial Lung Disease/Pneumonitis

Severe, life-threatening, and fatal interstitial lung disease (ILD) / pneumonitis can occur in patients treated with GAVRETO. Pneumonitis occurred in 12% of patients who received GAVRETO, including 3.3% with Grade 3-4, and 0.2% with fatal reactions.

Monitor for pulmonary symptoms indicative of ILD/pneumonitis. Withhold GAVRETO and promptly investigate for ILD in any patient who presents with acute or worsening of respiratory symptoms which may be indicative of ILD (e.g., dyspnea, cough, and fever). Withhold, reduce dose or permanently discontinue GAVRETO based on severity of confirmed ILD [see Dosage and Administration (2.3)].

5.3 Hypertension

Hypertension occurred in 35% of patients, including Grade 3 hypertension in 18% of patients [see Adverse Reactions (6.1)]. Overall, 8% had their dose interrupted and 4.8% had their dose reduced for hypertension. Treatment-emergent hypertension was most commonly managed with anti-hypertension medications.

Do not initiate GAVRETO in patients with uncontrolled hypertension. Optimize blood pressure prior to initiating GAVRETO. Monitor blood pressure after 1 week, at least monthly thereafter and as clinically indicated. Initiate or adjust anti-hypertensive therapy as appropriate. Withhold, reduce dose, or permanently discontinue GAVRETO based on the severity [see Dosage and Administration (2.3)].

5.4 Hepatotoxicity

Serious hepatic adverse reactions occurred in 1.5% of patients treated with GAVRETO. Increased AST occurred in 49% of patients, including Grade 3 or 4 in 7% and increased ALT occurred in 37% of patients, including Grade 3 or 4 in 4.8% [see Adverse Reactions (6.1)]. The median time to first onset for increased AST was 15 days (range: 5 days to 2.5 years) and for increased ALT was 24 days (range: 7 days to 3.7 years).

Monitor AST and ALT prior to initiating GAVRETO, every 2 weeks during the first 3 months, then monthly thereafter and as clinically indicated. Withhold, reduce dose or permanently discontinue GAVRETO based on severity [see Dosage and Administration (2.3)].

5.5 Hemorrhagic Events

Serious, including fatal, hemorrhagic events can occur with GAVRETO. Grade ≥ 3 hemorrhagic events occurred in 4.1% of patients treated with GAVRETO including one patient with a fatal hemorrhagic event.

Permanently discontinue GAVRETO in patients with severe or life-threatening hemorrhage [see Dosage and Administration (2.3)].

5.6 Tumor Lysis Syndrome

Cases of tumor lysis syndrome (TLS) have been reported in patients with medullary thyroid carcinoma receiving GAVRETO [see Adverse Reactions (6.1)]. Patients may be at risk of TLS if they have rapidly growing tumors, a high tumor burden, renal dysfunction, or dehydration. Closely monitor patients at risk, consider appropriate prophylaxis including hydration, and treat as clinically indicated.

5.7 Risk of Impaired Wound Healing

Impaired wound healing can occur in patients who receive drugs that inhibit the vascular endothelial growth factor (VEGF) signaling pathway. Therefore, GAVRETO has the potential to adversely affect wound healing.

Withhold GAVRETO for at least 5 days prior to elective surgery. Do not administer for at least 2 weeks following major surgery and until adequate wound healing. The safety of resumption of GAVRETO after resolution of wound healing complications has not been established.

5.8 Embryo-Fetal Toxicity

Based on findings from animal studies and its mechanism of action, GAVRETO can cause fetal harm when administered to a pregnant woman. Oral administration of pralsetinib to pregnant rats during the period of organogenesis resulted in malformations and embryolethality at maternal exposures below the human exposure at the clinical dose of 400 mg once daily.

Advise pregnant women of the potential risk to a fetus. Advise females of reproductive potential to use effective non-hormonal contraception during treatment with GAVRETO and for 2 weeks after the last dose. Advise males with female partners of reproductive potential to use effective contraception during treatment with GAVRETO and for 1 week after the last dose [see Use in Specific Populations (8.1, 8.3)].

6 ADVERSE REACTIONS

The following clinically significant adverse reactions are described elsewhere in the labeling:

- Serious Infections, Including Opportunistic Infections [see Warnings and Precautions (5.1)]
- Interstitial Lung Disease/Pneumonitis [see Warnings and Precautions (5.2)]
- Hypertension [see Warnings and Precautions (5.3)]
- Hepatotoxicity [see Warnings and Precautions (5.4)]
- Hemorrhagic Events [see Warnings and Precautions (5.5)]
- Tumor Lysis Syndrome [see Warnings and Precautions (5.6)]
- Risk of Impaired Wound Healing [see Warnings and Precautions (5.7)]
- Embryo-Fetal Toxicity [see Warnings and Precautions (5.8)]

6.1 Clinical Trials Experience

Because clinical trials are conducted under widely varying conditions, adverse reaction rates observed in the clinical trials of a drug cannot be directly compared to rates in the clinical trials of another drug and may not reflect the rates observed in practice.

The pooled safety population in the WARNINGS AND PRECAUTIONS reflect exposure to GAVRETO as a single agent at 400 mg orally once daily in 540 patients in ARROW [see Clinical Studies (14)]. Among 540 patients who received GAVRETO, 71% were exposed for 6 months or longer and 57% were exposed for greater than one year. The most common adverse reactions (≥ 25%) were musculoskeletal pain, constipation, hypertension, diarrhea, fatigue, edema, pyrexia, and cough. The most common Grade 3-4 laboratory abnormalities (≥ 2%) were decreased lymphocytes, decreased neutrophils, decreased hemoglobin, decreased phosphate, decreased leukocytes, decreased sodium, increased aspartate aminotransferase (AST), increased alanine aminotransferase (ALT), decreased calcium (corrected), decreased platelets, increased alkaline phosphatase, increased potassium, decreased potassium and increased bilirubin.

In addition to the 540 patients, certain subsections in the WARNINGS AND PRECAUTIONS describe adverse reactions observed with exposure to GAVRETO as a single agent in a randomized, open-label study, AcceleRET-Lung (NCT04222972), which enrolled 223 patients with RET-fusion positive locally advanced unresectable or metastatic NSCLC.

RET Fusion-Positive Non-Small Cell Lung Cancer

The safety of GAVRETO was evaluated as a single agent at 400 mg orally once daily in 281 patients with metastatic rearranged during transfection (RET fusion-positive) non-small cell lung cancer (NSCLC) in ARROW [see Clinical Studies (14.1)]. Among the 281 patients who received GAVRETO, 72% were exposed for 6 months or longer and 56% were exposed for ≥1 year.

The median age was 60 years (range: 26 to 87 years); 54% were female, 46% were White, 46% were Asian, and 4% were Hispanic/Latino.

Serious adverse reactions occurred in 65% of patients who received GAVRETO. The most frequent serious adverse reactions (in ≥ 2% of patients) were pneumonia, anemia, pneumonitis, pyrexia, sepsis, urinary tract infection, coronavirus infection, pleural effusion, dyspnea, musculoskeletal pain, pulmonary embolism, and seizure. Fatal adverse reactions occurred in 7% of patients; fatal adverse reactions which occurred in > 1 patient included pneumonia (n=8), sepsis (n=3) and COVID (n=3).

Permanent discontinuation due to an adverse reaction occurred in 20% of patients who received GAVRETO. Adverse reactions resulting in permanent discontinuation which occurred in ≥ 2% of patients included pneumonitis (3.2%), and pneumonia (2.8%).

Dosage interruptions due to an adverse reaction occurred in 73% of patients who received GAVRETO. Adverse reactions requiring dosage interruption in ≥ 2% of patients included anemia, pneumonia, pneumonitis, neutropenia, hypertension, increased blood creatine phosphokinase, fatigue, pyrexia, increased aspartate aminotransferase (AST), increased alanine aminotransferase (ALT), coronavirus infection, diarrhea, hypophosphatemia, musculoskeletal pain, thrombocytopenia, dyspnea, hemorrhage, leukopenia, lymphopenia, edema, sepsis, and vomiting.

Dose reductions due to adverse reactions occurred in 51% of patients who received GAVRETO. Adverse reactions requiring dosage reductions in ≥ 2% of patients included anemia, neutropenia, pneumonitis, increased blood creatine phosphokinase, leukopenia, hypertension, fatigue, pneumonia, and lymphopenia.

Table 5 summarizes the adverse reactions in patients with NSCLC in ARROW.

Table 5: Adverse Reactions (≥ 15%) in RET Fusion-Positive NSCLC Patients Who Received GAVRETO in ARROW
Adverse reaction | GAVRETO N = 281
Adverse reaction | Grades 1 - 4 (%) | Grades 3 or 4 (%)
Gastrointestinal disorders
Constipation | 45 | 0.7
Diarrhea | 30 | 2.5
Nausea | 19 | 0
Dry mouth | 17 | 0
General Disorders and Administration Site Conditions
Edema [Includes the preferred terms: Edema, Swelling face, Peripheral swelling, Generalized oedema, Edema peripheral, Face edema, Periorbital edema, Eyelid edema, Swelling, Localized edema] | 44 | 0
Fatigue [Includes the preferred terms: Fatigue, Asthenia] | 42 | 2.5
Pyrexia | 29 | 0.7
Musculoskeletal and Connective Tissue Disorders
Musculoskeletal pain [Includes the preferred terms: Myalgia, Arthralgia, Pain in extremity, Neck pain, Musculoskeletal pain, Back pain, Musculoskeletal chest pain, Bone pain, Musculoskeletal stiffness] | 44 | 2.5
Increased Blood Creatine Phosphokinase | 19 | 9
Vascular
Hypertension [Includes the preferred terms: Hypertension, Blood pressure increased] | 38 | 18
Respiratory, thoracic and mediastinal disorders
Cough [Includes the preferred terms: Cough, Productive Cough, Upper-airway cough syndrome] | 36 | 0.4
Dyspnea | 21 | 2.1
Infection and Infestations
Pneumonia [Includes the preferred terms: Pneumonia, Pneumocystis jirovecii pneumonia, Pneumonia cytomegaloviral, Atypical pneumonia, Lung infection, Pneumonia bacterial, Pneumonia hemophilus, Pneumonia influenzal, Pneumonia streptococcal, Pneumonia viral, Pneumonia pseudomonal] | 24 | 13
Urinary tract infection | 16 | 3.6
Metabolism and Nutrition Disorders
Decreased appetite | 18 | 1.1
Nervous system disorders
Taste disorder [Includes the preferred terms: Dysgeusia, Ageusia] | 17 | 0
Headache [Includes the preferred terms: Headache, Tension Headache] | 15 | 1.1
Skin and subcutaneous tissue disorders
Rash [Includes the preferred terms: Rash, Rash maculo-papular, Dermatitis acneiform, Erythema, Rash generalized, Rash papular, Rash macular, Rash erythematous] | 17 | 0

Clinically relevant adverse reactions occurring in < 15% of patients included pneumonitis (14%), vomiting (14%), abdominal pain (14%), and stomatitis (6%).

Table 6 summarizes the laboratory abnormalities in ARROW.

Table 6: Select Laboratory Abnormalities (≥ 20%) Worsening from Baseline in RET Fusion-Positive NSCLC Patients Who Received GAVRETO in ARROW
Laboratory Abnormality | GAVRETO N=281
Laboratory Abnormality | Grades 1-4 (%) | Grades 3-4 (%)
Chemistry
Increased AST | 80 | 3.2
Increased ALT | 58 | 3.9
Decreased albumin | 52 | 0
Decreased calcium (corrected) | 50 | 1.8
Decreased phosphate | 50 | 17
Increased creatinine | 45 | 1.4
Increased alkaline phosphatase | 43 | 2.5
Decreased sodium | 42 | 10
Decreased Potassium | 27 | 4.6
Increased Potassium | 27 | 1.8
Decreased Magnesium | 25 | 0
Increased Bilirubin | 20 | 1.8
Hematology
Decreased leukocytes | 79 | 11
Decreased hemoglobin | 78 | 18
Decreased lymphocytes | 73 | 32
Decreased neutrophils | 70 | 21
Decreased platelets | 33 | 5

Clinically relevant laboratory abnormalities occurring in < 20% of patients who received GAVRETO included increased magnesium (14%).

RET-altered Thyroid Cancer

The safety of GAVRETO was evaluated as a single agent at 400 mg orally once daily in 138 patients with RET-altered Thyroid Cancer (including 19 patients with RET fusion-positive thyroid cancer) in ARROW [see Clinical Studies (14.2)]. Among the 138 patients who received GAVRETO, 68% were exposed for 6 months or longer, and 40% were exposed for greater than one year.

The median age was 59 years (range: 18 to 83 years); 36% were female, 74% were White, 17% were Asian, and 6% were Hispanic/Latino.

Serious adverse reactions occurred in 39% of patients who received GAVRETO. The most frequent serious adverse reactions (in ≥ 2% of patients) were pneumonia, pneumonitis, urinary tract infection, pyrexia, fatigue, diarrhea, dizziness, anemia, hyponatremia, and ascites. Fatal adverse reaction occurred in 2.2% of patients; fatal adverse reactions that occurred in > 1 patient included pneumonia (n=2).

Permanent discontinuation due to an adverse reaction occurred in 9% of patients who received GAVRETO. Adverse reactions resulting in permanent discontinuation which occurred in > 1 patient included fatigue, pneumonia and anemia.

Dosage interruptions due to an adverse reaction occurred in 67% of patients who received GAVRETO. Adverse reactions requiring dosage interruption in ≥ 2% of patients included neutropenia, hypertension, diarrhea, fatigue, pneumonitis, anemia, increased blood creatine phosphokinase, pneumonia, urinary tract infection, musculoskeletal pain, vomiting, pyrexia, increased AST, dyspnea, hypocalcemia, cough, thrombocytopenia, abdominal pain, increased blood creatinine, dizziness, headache, decreased lymphocyte count, stomatitis, and syncope.

Dose reductions due to adverse reactions occurred in 44% of patients who received GAVRETO. Adverse reactions requiring dosage reductions in ≥ 2% of patients included neutropenia, anemia, hypertension, increased blood creatine phosphokinase, decreased lymphocyte count, pneumonitis, fatigue and thrombocytopenia.

Table 7 summarizes the adverse reactions occurring in RET-altered Thyroid Cancer Patients in ARROW.

Table 7: Adverse Reactions (≥ 15%) in RET-altered Thyroid Cancer Patients Who Received GAVRETO in ARROW
Adverse Reactions | GAVRETO N=138
Adverse Reactions | Grades 1-4 (%) | Grades 3-4 (%)
Musculoskeletal
Musculoskeletal Pain [Musculoskeletal Pain includes arthralgia, arthritis, back pain, bone pain, musculoskeletal chest pain, musculoskeletal pain, musculoskeletal stiffness, myalgia, neck pain, non-cardiac chest pain, pain in extremity, spinal pain] | 42 | 0.7 [Only includes a Grade 3 adverse reaction]
Gastrointestinal
Constipation | 41 | 0.7
Diarrhea [Diarrhea includes colitis, diarrhea] | 34 | 5
Abdominal Pain [Abdominal Pain includes abdominal discomfort, abdominal pain, abdominal pain upper, abdominal tenderness, epigastric discomfort] | 17 | 0.7
Dry mouth | 17 | 0
Stomatitis [Stomatitis includes mucosal inflammation, stomatitis, tongue ulceration] | 17 | 0.7
Nausea | 17 | 0.7
Vascular
Hypertension | 40 | 21
General
Fatigue [Fatigue includes asthenia, fatigue] | 38 | 6
Edema [Edema includes eyelid edema, face edema, edema, edema peripheral, periorbital edema] | 29 | 0
Pyrexia | 22 | 2.2
Respiratory
Cough [Cough includes cough, productive cough, upper-airway cough syndrome] | 27 | 1.4
Dyspnea [Dyspnea includes dyspnea, dyspnea exertional] | 22 | 2.2
Nervous System
Headache [Headache includes headache, migraine] | 24 | 0
Peripheral Neuropathy [Peripheral neuropathy includes dysaesthesia, hyperaesthesia, hypoaesthesia, neuralgia, neuropathy peripheral, paraesthesia, peripheral sensory neuropathy, polyneuropathy] | 20 | 0
Dizziness [Dizziness includes dizziness, dizziness postural, vertigo] | 19 | 0.7
Dysgeusia [Dysgeusia includes ageusia, dysgeusia] | 17 | 0
Skin and Subcutaneous
Rash [Rash includes dermatitis, dermatitis acneiform, eczema, palmar-plantar, erythrodysaesthesia syndrome, rash, rash erythematous, rash macular, rash maculo-papular, rash papular, rash pustular] | 24 | 0
Metabolism and Nutrition
Decreased Appetite | 15 | 0

Clinically relevant adverse reactions in < 15% of patients who received GAVRETO included tumor lysis syndrome and increased creatine phosphokinase.

Table 8 summarizes the laboratory abnormalities occurring in RET-altered Thyroid Cancer Patients in ARROW.

Table 8: Select Laboratory Abnormalities (≥ 20%) Worsening from Baseline in RET-altered Thyroid Cancer Patients Who Received GAVRETO in ARROW
Laboratory Abnormality | GAVRETO N=138
Laboratory Abnormality | Grades 1-4 (%) | Grades 3-4 (%)
Chemistry
Decreased calcium (corrected) | 70 | 9
Increased AST | 69 | 4.3
Increased ALT | 43 | 3.6
Increased creatinine | 41 | 0
Decreased albumin | 41 | 1.5
Decreased sodium | 28 | 2.2
Decreased phosphate | 28 | 8
Decreased magnesium | 27 | 0.7
Increased potassium | 26 | 1.4
Increased bilirubin | 24 | 1.4
Increased alkaline phosphatase | 22 | 1.4
Hematology
Decreased lymphocytes | 67 | 27
Decreased hemoglobin | 63 | 13
Decreased neutrophils | 59 | 16
Decreased platelets | 31 | 2.9
Denominator for each laboratory parameter is based on the number of patients with a baseline and post-treatment laboratory value available, which ranged from 135 to 138 patients.

Clinically relevant laboratory abnormalities in patients who received GAVRETO included increased phosphate (40%).

Other Clinical Trials Experience

AcceleRET-Lung trial (NCT04222972)

In AcceleRET-Lung trial (NCT04222972), single agent GAVRETO (n=108) was compared to chemotherapy/immunotherapy (n=104) in patients with RET fusion-positive NSCLC. Adverse reactions were infections (72% vs.52%), including pneumonia (29% vs. 6%), urinary tract infection (22% vs. 8%), and opportunistic infections (20% vs. 6%). Opportunistic infections included pneumocystis jirovecii pneumonia, fungal infections, legionella pneumonia, cytomegalovirus infection, and herpes simplex.

7 DRUG INTERACTIONS

7.1 Effects of Other Drugs on GAVRETO

Strong or Moderate CYP3A and/or P-gp Inhibitors

Concomitant use with a strong or moderate CYP3A inhibitor and/or a P-gp inhibitor increases pralsetinib exposure [Clinical Pharmacology (12.3)], which may increase the risk of adverse reactions related to GAVRETO. Avoid coadministration of GAVRETO with a strong or moderate CYP3A and/or P-gp inhibitor. If coadministration with any of the above inhibitors cannot be avoided, reduce the GAVRETO dose [see Dosage and Administration (2.4)].

Strong or Moderate CYP3A Inducers

Concomitant use with a strong CYP3A inducer decreases pralsetinib exposure [see Clinical Pharmacology (12.3)], which may decrease efficacy of GAVRETO. Avoid concomitant use of GAVRETO with strong or moderate CYP3A inducers. If coadministration of GAVRETO with strong or moderate CYP3A inducers cannot be avoided, increase the GAVRETO dose [see Dosage and Administration (2.5)]

8 USE IN SPECIFIC POPULATIONS

8.1 Pregnancy

Risk Summary

Based on findings from animal studies and its mechanism of action, GAVRETO can cause fetal harm when administered to a pregnant woman [see Clinical Pharmacology (12.1)]. There are no available data on GAVRETO use in pregnant women to inform drug-associated risk. Oral administration of pralsetinib to pregnant rats during the period of organogenesis resulted in malformations and embryolethality at maternal exposures below the human exposure at the clinical dose of 400 mg once daily (see Data). Advise pregnant women of the potential risk to a fetus.

In the U.S. general population, the estimated background risk of major birth defects and miscarriage in clinically recognized pregnancies is 2-4% and 15-20%, respectively.

Data

Animal Data

In an embryo-fetal development study, once daily oral administration of pralsetinib to pregnant rats during the period of organogenesis resulted in 100% post-implantation loss at dose levels ≥ 20 mg/kg (approximately 1.8 times the human exposure based on area under the curve [AUC] at the clinical dose of 400 mg). Post-implantation loss also occurred at the 10 mg/kg dose level (approximately 0.6 times the human exposure based on AUC at the clinical dose of 400 mg). Once daily oral administration of pralsetinib at dose levels ≥ 5 mg/kg (approximately 0.2 times the human AUC at the clinical dose of 400 mg) resulted in an increase in visceral malformations and variations (absent or small kidney and ureter, absent uterine horn, malpositioned kidney or testis, retroesophageal aortic arch) and skeletal malformations and variations (vertebral and rib anomalies and reduced ossification).

8.2 Lactation

Risk Summary

There are no data on the presence of pralsetinib or its metabolites in human milk or their effects on either the breastfed child or on milk production. Because of the potential for serious adverse reactions in breastfed children, advise women not to breastfeed during treatment with GAVRETO and for 1 week after the last dose.

8.3 Females and Males of Reproductive Potential

Based on animal data, GAVRETO can cause embryolethality and malformations at doses resulting in exposures below the human exposure at the clinical dose of 400 mg daily [see Use in Specific Populations (8.1)].

Pregnancy Testing

Verify pregnancy status of females of reproductive potential prior to initiating GAVRETO [see Use in Specific Populations (8.1)].

Contraception

GAVRETO can cause fetal harm when administered to a pregnant woman [see Use in Specific Populations (8.1)].

Females

Advise females of reproductive potential to use effective non-hormonal contraception during treatment with GAVRETO and for 2 weeks after the last dose. GAVRETO may render hormonal contraceptives ineffective.

Males

Advise males with female partners of reproductive potential to use effective contraception during treatment with GAVRETO and for 1 week after the last dose.

Infertility

Based on histopathological findings in the reproductive tissues of male and female rats and a dedicated fertility study in which animals of both sexes were treated and mated to each other, GAVRETO may impair fertility [see Nonclinical Toxicology (13.1)].

8.4 Pediatric Use

The safety and effectiveness of GAVRETO have been established in pediatric patients aged 12 years and older for RET fusion-positive thyroid cancer. Use of GAVRETO in this age group is supported by evidence from an adequate and well-controlled study of GAVRETO in adults with additional population pharmacokinetic data demonstrating that age and body weight had no clinically meaningful effect on the pharmacokinetics of pralsetinib, that the exposure of pralsetinib is expected to be similar between adults and pediatric patients age 12 years and older, and that the course of RET fusion-positive thyroid cancer is sufficiently similar in adults and pediatric patients to allow extrapolation of data in adults to pediatric patients [see Adverse Reactions (6.1), Clinical Pharmacology (12.3), and Clinical Studies (14.2)].

The safety and effectiveness of GAVRETO have not been established in pediatric patients with RET fusion-positive NSCLC or in pediatric patients younger than 12 years old with RET fusion-positive thyroid cancer.

Animal Toxicity Data

In a 4-week repeat-dose toxicology study in non-human primates, physeal dysplasia in the femur occurred at doses resulting in exposures similar to the human exposure (AUC) at the clinical dose of 400 mg. In rats there were findings of increased physeal thickness in the femur and sternum as well as tooth (incisor) abnormalities (fractures, dentin matrix alteration, ameloblast/odontoblast degeneration, necrosis) in both 4- and 13-week studies at doses resulting in exposures similar to the human exposure (AUC) at the clinical dose of 400 mg. Recovery was not assessed in the 13-week toxicology study, but increased physeal thickness in the femur and incisor degeneration did not show evidence of complete recovery in the 28-day rat study.

Monitor growth plates in adolescent patients with open growth plates. Consider interrupting or discontinuing therapy based on the severity of any growth plate abnormalities and based on an individual risk-benefit assessment.

8.5 Geriatric Use

Of the 540 patients in ARROW who received the recommended dose of GAVRETO at 400 mg once daily, 31% were 65 years or and over, while 7% were 75 years and over.

No overall differences in pharmacokinetics (PK), safety or effectiveness were observed between patients aged 65 years or older and younger patients.

8.6 Hepatic Impairment

No dose adjustment is required for patients with mild (total bilirubin ≤ ULN and AST > ULN or total bilirubin > 1 to 1.5 × ULN and any AST), moderate (total bilirubin > 1.5 to 3 × ULN and any AST) or severe (total bilirubin > 3 × ULN and any AST) hepatic impairment .

11 DESCRIPTION

Pralsetinib is an oral receptor tyrosine kinase inhibitor. The chemical name for pralsetinib is (cis)- N-((S)-1-(6-(4-fluoro-1 H-pyrazol-1-yl)pyridin-3-yl)ethyl)-1-methoxy-4-(4-methyl-6-(5-methyl-1 H-pyrazol-3-ylamino)pyrimidin-2-yl)cyclohexanecarboxamide. The molecular formula for pralsetinib is C27H32FN9O2, and the molecular weight is 533.61 g/mol. Pralsetinib has the following structure:

The solubility of pralsetinib in aqueous media decreases over the range pH 1.99 to pH 7.64 from 0.880 mg/mL to < 0.001 mg/mL, indicating a decrease in solubility with increasing pH.

GAVRETO (pralsetinib) is supplied for oral use as immediate release hydroxypropyl methylcellulose (HPMC) hard capsules containing 100 mg pralsetinib. The capsules also contain inactive ingredients:

citric acid, hydroxypropyl methylcellulose (HPMC), magnesium stearate, microcrystalline cellulose (MCC), pregelatinized starch and sodium bicarbonate. The capsule shell consists of FD&C Blue #1 (Brilliant Blue FCF), hypromellose and titanium dioxide. The white printing ink contains butyl alcohol, dehydrated alcohol, isopropyl alcohol, potassium hydroxide, propylene glycol, purified water, shellac, strong ammonia solution and titanium dioxide.

12 CLINICAL PHARMACOLOGY

12.1 Mechanism of Action

Pralsetinib is a kinase inhibitor of wild-type RET and oncogenic RET fusions (CCDC6-RET) and mutations (RET V804L, RET V804M and RET M918T) with half maximal inhibitory concentrations (IC50s) less than 0.5 nM. In purified enzyme assays, pralsetinib inhibited DDR1, TRKC, FLT3, JAK1-2, TRKA, VEGFR2, PDGFRB, and FGFR1 at higher concentrations that were still clinically achievable at Cmax. In cellular assays, pralsetinib inhibited RET at approximately 14-, 40-, and 12-fold lower concentrations than VEGFR2, FGFR2, and JAK2, respectively.

Certain RET fusion proteins and activating point mutations can drive tumorigenic potential through hyperactivation of downstream signaling pathways leading to uncontrolled cell proliferation. Pralsetinib exhibited anti-tumor activity in cultured cells and animal tumor implantation models harboring oncogenic RET fusions or mutations including KIF5B-RET, CCDC6-RET, RET M918T, RET C634W, RET V804E, RET V804L and RET V804M. In addition, pralsetinib prolonged survival in mice implanted intracranially with tumor models expressing KIF5B-RET or CCDC6-RET.

12.2 Pharmacodynamics

Pralsetinib exposure-response relationships and the time course of pharmacodynamics response have not been fully characterized.

Cardiac Electrophysiology

The QT interval prolongation potential of pralsetinib was assessed in 34 patients with RET-altered solid tumors administered GAVRETO at the recommended dosage. No large mean increase in QTc (> 20 ms) was detected in the study.

12.3 Pharmacokinetics

At 400 mg GAVRETO once daily under fasting conditions, the steady state mean [% coefficient of variation (CV%)] of maximum observed plasma concentration (Cmax) and area under the concentration-time curve (AUC0-24h) of pralsetinib was 2,470 (55%) ng/mL and 36,700 (66%) h•ng/mL, respectively. Pralsetinib Cmax and AUC increased inconsistently over the dose range of 60 mg to 600 mg once daily (0.15 to 1.5 times the recommended dose). Pralsetinib plasma concentrations reached steady state by 3 to 5 days. The mean accumulation ratio was approximately 2-fold after once-daily oral administration.

Absorption

The median time to peak concentration (Tmax) ranged from 2 to 4 hours following single doses of pralsetinib 60 mg to 600 mg.

Food Effect

Following administration of a single dose of 200 mg with a high-fat meal, (approximately 800 to 1000 calories with 50 to 60% of calories from fat), the mean Cmax of pralsetinib was increased by 2.0-fold, the mean AUC0-INF was increased by 2.2-fold, and the median Tmax was delayed from 4 to 8.5 hours, compared to the fasted state.

Distribution

The mean (CV%) apparent volume of distribution (Vd/F) of pralsetinib is 303 L (68%). Protein binding of pralsetinib is 97% and is independent of concentration. The blood-to-plasma ratio is 0.6 to 0.7.

Elimination

The mean (±standard deviation) plasma elimination half-life (T½) of pralsetinib is 16 hours (10) following single doses and 20 hours (12) following multiple doses of pralsetinib. The mean (CV%) apparent oral clearance (CL/F) of pralsetinib is 11 L/h (66%) at steady state.

Metabolism

Pralsetinib is primarily metabolized by CYP3A4 and to a lesser extent by CYP2D6 and CYP1A2, in vitro. Following a single oral dose of 310 mg of radiolabeled pralsetinib, pralsetinib metabolites from oxidation and glucuronidation were detected as 5% or less.

Excretion

Approximately 73% (66% as unchanged) of the total administered radioactive dose [^14C] pralsetinib was recovered in feces and 6% (4.8% as unchanged) was recovered in urine.

Specific Populations

No clinically significant differences in the PK of pralsetinib were observed based on age (19 to 87 years), sex, race (White, Black, or Asian), and body weight (32 to 128 kg). Mild and moderate renal impairment (CLcr 30 - 89 mL/min) had no effect on the exposure of pralsetinib. Pralsetinib has not been studied in patients with severe renal impairment (CLcr < 15 mL/min).

Drug Interaction Studies

Clinical Studies and Model-Informed Approach

CYP3A Inhibitors: Coadministration of multiple doses of CYP3A inhibitors increases pralsetinib Cmax and AUC.

Table 9: Observed or Predicted Increase in Pralsetinib Exposure after Coadministration of CYP3A Inhibitors
Type of inhibitor | Coadministered CYP3A Inhibitor | Increase in pralsetinib Cmax | Increase in pralsetinib AUC
 |  | Observed
P-gp and Strong CYP3A Inhibitor | Itraconazole (200 mg twice daily on Day 1, followed by 200 mg once daily) | 1.8-fold | 3.5-fold
 |  | Predicted
Strong CYP3A Inhibitors | Voriconazole (400 mg twice daily on Day 1, followed by 200 mg twice daily) | 1.2-fold | 2.2-fold
Combined P-gp and Moderate CYP3A Inhibitors | Verapamil (80 mg three times daily) | 1.6-fold | 2.1-fold
Moderate CYP3A Inhibitors | Fluconazole (400 mg once daily) | 1.2-fold | 1.7-fold

P-gp Inhibitors: Coadministration of cyclosporine (single 600 mg dose) with a single 200 mg dose of pralsetinib in healthy subjects increased pralsetinib AUC0-inf by 1.8-fold and Cmax by 1.5-fold, relative to a 200 mg dose of pralsetinib administered alone.

Strong CYP3A Inducers: Coadministration of rifampin 600 mg once daily with a single GAVRETO 400 mg dose decreased pralsetinib AUC0-INF by 68% and Cmax by 30%.

Moderate CYP3A Inducers: Coadministration of multiple doses of efavirenz (600 mg once daily) is predicted to decrease the pralsetinib AUC by 45% and Cmax by 18%.

Mild CYP3A Inducers: No clinically significant differences in the PK of pralsetinib were identified when GAVRETO was coadministered with mild CYP3A inducers.

Acid-Reducing Agents: No clinically significant differences in the PK of pralsetinib were observed when GAVRETO was coadministered with gastric acid reducing agents.

In Vitro Studies

Cytochrome P450 (CYP) Enzymes: Pralsetinib is a time-dependent inhibitor of CYP3A and an inhibitor of CYP2C8, CYP2C9, and CYP3A, but not an inhibitor of CYP1A2, CYP2B6, CYP2C19 or CYP2D6 at clinically relevant concentrations.

Pralsetinib is an inducer of CYP2C8, CYP2C9, and CYP3A, but not an inducer of CYP1A2, CYP2B6, or CYP2C19 at clinically relevant concentrations.

Transporter Systems: Pralsetinib is a substrate of P-gp and BCRP, but not a substrate of BSEP, OCT1, OCT2, OATP1B1, OATP1B3, MATE1, MATE2-K, OAT1, or OAT3.

Pralsetinib is an inhibitor of P-gp, BCRP, OATP1B1, OATP1B3, OAT1, MATE1, MATE2-K, and BSEP, but not an inhibitor of OCT1, OCT2, and OAT1A3 at clinically relevant concentrations.

13 NONCLINICAL TOXICOLOGY

13.1 Carcinogenesis, Mutagenesis, Impairment of Fertility

Carcinogenicity studies with pralsetinib have not been conducted. Pralsetinib was not mutagenic in an in vitro bacterial reverse mutation (Ames) assay with or without metabolic activation and was not clastogenic in either an in vitro micronucleus assay in TK6 cells or an in vivo bone marrow micronucleus assay in rats.

In a dedicated fertility and early embryonic development study conducted in treated male rats mated to treated female rats, although pralsetinib did not have clear effects on male or female mating performance or ability to become pregnant, at the 20 mg/kg dose level (approximately 2.9 times the human exposure (AUC) at the clinical dose of 400 mg based on toxicokinetic data from the 13-week rat toxicology study) 82% of female rats had totally resorbed litters, with 92% post-implantation loss (early resorptions); post-implantation loss occurred at doses as low as 5 mg/kg (approximately 0.35 times the human exposure (AUC) at the clinical dose of 400 mg based on toxicokinetic data from the 13-week rat toxicology study). In a separate fertility and early embryonic development study in which male rats administered 20 mg/kg pralsetinib were mated to untreated female rats, there were no clear pralsetinib-related effects on intrauterine survival of embryos or on male reproductive performance at a dose approximately 1.7 times the human exposure (AUC) at the clinical dose of 400 mg. In a 13-week repeat-dose toxicology study, male rats exhibited histopathological evidence of tubular degeneration/atrophy in the testis with secondary cellular debris and reduced sperm in the lumen of the epididymis, which correlated with lower mean testis and epididymis weights and gross observations of soft and small testis. Female rats exhibited degeneration of the corpus luteum in the ovary. For both sexes, these effects were observed at pralsetinib doses ≥ 10 mg/kg/day, approximately 1 times the human exposure based on AUC at the clinical dose of 400 mg.

13.2 Animal Toxicology and/or Pharmacology

In 28-day rat and monkey toxicology studies, once daily oral administration of pralsetinib resulted in histologic necrosis and hemorrhage in the heart of preterm decedents at exposures ≥ 1.3 times and ≥ 3.1 times, respectively, the human exposure based on AUC at the clinical dose of 400 mg. Pralsetinib induced hyperphosphatemia (rats) and multi-organ mineralization (rats and monkeys) in 13-week toxicology studies at exposures approximately 2.8 times and ≥ 0.13 times, respectively, the human exposure based on AUC at the clinical dose of 400 mg.

14 CLINICAL STUDIES

14.1 Metastatic RET Fusion-Positive Non-Small Cell Lung Cancer

The efficacy of GAVRETO was evaluated in patients with RET fusion-positive metastatic NSCLC in a multicenter, non-randomized, open-label, multi-cohort clinical trial (ARROW, NCT03037385). The study enrolled, in separate cohorts, patients with metastatic RET fusion-positive NSCLC who had progressed on platinum-based chemotherapy and treatment-naïve patients with metastatic NSCLC. Identification of a RET gene fusion was determined by local laboratories using next generation sequencing (NGS), fluorescence in situ hybridization (FISH), and other tests. Among the 237 patients in the efficacy population(s) described in this section, samples from 40% of patients were retrospectively tested with the LIFE Technologies Corporation Oncomine Dx Target Test (ODxTT). Patients with asymptomatic central nervous system (CNS) metastases, including patients with stable or decreasing steroid use within 2 weeks prior to study entry, were enrolled. Patients received GAVRETO 400 mg orally once daily until disease progression or unacceptable toxicity.

The major efficacy outcome measures were overall response rate (ORR) and duration of response (DOR), as assessed by a blinded independent central review (BICR) according to RECIST v1.1.

Metastatic RET Fusion-Positive NSCLC Previously Treated with Platinum Chemotherapy

Efficacy was evaluated in 130 patients with RET fusion-positive NSCLC with measurable disease who were previously treated with platinum chemotherapy enrolled into a cohort of ARROW.

The median age was 59 years (range: 26 to 85); 51% were female, 40% were White, 50% were Asian, 4.6% were Hispanic/Latino. ECOG performance status was 0-1 (95%) or 2 (3.8%), 99% of patients had metastatic disease, and 41% had either a history of or current CNS metastasis. Patients received a median of 2 prior systemic therapies (range 1–6); 42% had prior anti-PD-1/PD-L1 therapy and 27% had prior kinase inhibitors. A total of 48% of the patients received prior radiation therapy. RET fusions were detected in 80% of patients using NGS (37% tumor samples; 15% blood or plasma samples, 28% unknown), 13% using FISH, and 2% using other methods. The most common RET fusion partners were KIF5B (70%) and CCDC6 (19%).

Efficacy results for RET fusion-positive NSCLC patients who received prior platinum-based chemotherapy are summarized in Table 10.

Table 10: Efficacy Results in ARROW (Metastatic RET Fusion-Positive NSCLC Previously Treated with Platinum Chemotherapy)
Efficacy Parameter | GAVRETO N=130
Overall Response Rate (ORR) [Confirmed overall response rate assessed by BICR] (95% CI) | 63 (54, 71)
Complete Response, % | 6
Partial Response, % | 57
Duration of Response (DOR) | N=82
Median, months (95% CI) | 38.8 (14.8, NE)
Patients with DOR ≥ 12-months [Based on observed duration of response] , % | 66
NE = not estimable

For the 54 patients who received an anti-PD-1 or anti-PD-L1 therapy, either sequentially or concurrently with platinum-based chemotherapy, an exploratory subgroup analysis of ORR was 59% (95% CI: 45, 72) and the median DOR was 22.3 months (95% CI: 8.0, NE).

Among the 130 patients with RET fusion-positive NSCLC, 10 had measurable CNS metastases at baseline as assessed by BICR. No patients received radiation therapy (RT) to the brain within 2 months prior to study entry. Responses in intracranial lesions were observed in 7 of these 10 patients including 2 patients with a CNS complete response; 71% of responders had a DOR of ≥ 6 months.

Treatment-naïve RET Fusion-Positive NSCLC

Efficacy was evaluated in 107 patients with treatment-naïve RET fusion-positive NSCLC with measurable disease enrolled into ARROW.

The median age was 62 years (range 30 to 87); 53% were female, 49% were White, 45% were Asian, and 2.8% were Hispanic or Latino. ECOG performance status was 0-1 for 99% of the patients and 98% of patients had metastatic disease; 28% had either history of or current CNS metastasis. RET fusions were detected in 68% of patients using NGS (30% tumor samples; 17% blood or plasma; 22% unknown) and 19% using FISH. The most common RET fusion partners were KIF5B (71%) and CCDC6 (18%).

Efficacy results for treatment-naïve RET fusion-positive NSCLC are summarized in Table 11.

Table 11: Efficacy Results for ARROW (Treatment-Naïve Metastatic RET Fusion-Positive NSCLC)
Efficacy Parameter | GAVRETO N=107
Overall Response Rate (ORR) [Confirmed overall response rate assessed by BICR] (95% CI) | 78 (68, 85)
Complete Response, % | 7
Partial Response, % | 71
Duration of Response (DOR) | N=83
Median, months (95% CI) | 13.4 (9.4, 23.1)
Patients with DOR ≥ 12-months [Based on observed duration of response] , % | 45

14.2 RET Fusion-Positive Thyroid Cancer

The efficacy of GAVRETO was evaluated in RET fusion-positive metastatic thyroid cancer patients in a multicenter, open-label, multi-cohort clinical trial (ARROW, NCT03037385). All patients with RET fusion-positive thyroid cancer were required to have disease progression following standard therapy, measurable disease by RECIST version 1.1, and have RET fusion status as detected by local testing (89% NGS tumor samples and 11% using FISH).

The median age was 61 years (range: 46 to 74); 67% were male, 78% were White, 22% were Asian, 11% were Hispanic/Latino. All patients (100%) had papillary thyroid cancer. ECOG performance status was 0-1 (100%), all patients (100%) had metastatic disease, and 56% had a history of CNS metastases. Patients had received a median of 2 prior therapies (range 1-8). Prior systemic treatments included prior radioactive iodine (100%) and prior sorafenib and/or lenvatinib (56%).

Efficacy results are summarized in Table 12.

Table 12: Efficacy Results for RET Fusion-Positive Thyroid Cancer (ARROW)
Efficacy Parameters | GAVRETO N=9
Overall Response Rate (ORR) [Confirmed overall response rate assessed by BICR] (95% CI) | 89 (52, 100)
Complete Response, % | 0
Partial Response, % | 89
Duration of Response (DOR) | N=8
Median in months (95% CI) | NR (NE, NE)
Patients with DOR ≥ 6 months [Based on observed duration of response] , % | 100
NR = Not Reached; NE = Not Estimable

16 HOW SUPPLIED/STORAGE AND HANDLING

GAVRETO (pralsetinib) 100 mg, light blue, opaque, immediate release, hydroxypropyl methylcellulose (HPMC) hard capsule printed with "BLU-667" on the capsule shell body and "100 mg" on the capsule shell cap are supplied as follows:

- Bottles of 60 capsules (NDC 71332-006-60).
- Bottles of 90 capsules (NDC 71332-006-90).
- Bottles of 120 capsules (NDC 71332-006-12).

STORAGE AND HANDLING

Store at 20°C to 25°C (68°F to 77°F); excursions are permitted from 15°C to 30°C (59°F to 86°F) [see USP Controlled Room Temperature]. Protect from moisture.

17 PATIENT COUNSELING INFORMATION

Advise the patient to read the FDA-approved patient labeling (Medication Guide).

Serious Infections, Including Opportunistic Infections

Advise patients that GAVRETO may increase the risk of serious infections and to contact their healthcare provider if they experience symptoms of infections [see Warnings and Precautions (5.1)].

ILD/Pneumonitis

Advise patients to contact their healthcare provider if they experience new or worsening respiratory symptoms [see Warnings and Precautions (5.2)].

Hypertension

Advise patients that they will require regular blood pressure monitoring and to contact their healthcare provider if they experience symptoms of increased blood pressure or elevated readings [see Warnings and Precautions (5.3)].

Hepatotoxicity

Advise patients that hepatotoxicity can occur and to immediately contact their healthcare provider for signs or symptoms of hepatotoxicity [see Warnings and Precautions (5.4)].

Hemorrhagic Events

Advise patients that GAVRETO may increase the risk for bleeding and to contact their healthcare provider if they experience any signs or symptoms of bleeding [see Warnings and Precautions (5.5)].

Tumor Lysis Syndrome

Advise patients to contact their healthcare provider promptly to report any signs and symptoms of TLS [see Warnings and Precautions (5.6)].

Risk of Impaired Wound Healing

Advise patients that GAVRETO may impair wound healing. Advise patients that temporary interruption of GAVRETO is recommended prior to any elective surgery [see Warnings and Precautions (5.7)].

Embryo-Fetal Toxicity

Advise females of reproductive potential of the potential risk to a fetus. Advise females of reproductive potential to inform their healthcare provider of a known or suspected pregnancy [see Warnings and Precautions (5.8), Use in Specific Populations (8.1)].

Advise females of reproductive potential to use effective non-hormonal contraception during the treatment with GAVRETO and for 2 weeks after the last dose [see Use in Specific Populations (8.3)].

Advise males with female partners of reproductive potential to use effective contraception during treatment with GAVRETO and for 1 week after the last dose [see Use in Specific Populations (8.3)].

Lactation

Advise women not to breastfeed during treatment with GAVRETO and for 1 week after the last dose [see Use in Specific Populations (8.2)].

Infertility

Advise males and females of reproductive potential that GAVRETO may impair fertility [See Use in Specific Populations (8.3)].

Drug Interactions

Advise patients and caregivers to inform their healthcare provider of all concomitant medications, including prescription medicines, over-the-counter drugs, vitamins, and herbal products [see Drug Interactions (7.1)].

Administration

Advise patients to take GAVRETO on an empty stomach (no food intake for at least 2 hours before and at least 1 hour after taking GAVRETO) [see Dosage and Administration (2.2)].

GAVRETO® [pralsetinib]

Manufactured for:

Rigel Pharmaceuticals, Inc.
South San Francisco, CA 94080

GAVRETO® is a registered trademark of Rigel Pharmaceuticals, Inc.

For more information go to www.GAVRETO.com or call 1-800-983-1329.

12/2025

MEDICATION GUIDE
GAVRETO (gav-REH-toh)
(pralsetinib)
capsules, for oral use

What is the most important information I should know about GAVRETO?
GAVRETO may cause serious side effects, including:

- Serious infections. GAVRETO may increase your risk for serious infections, including infections caused by bacteria, fungi, or viruses, or infections that can happen when your immune system is weak (opportunistic infections). These serious infections can lead to hospitalization or death. Tell your healthcare provider right away if you get symptoms of an infection, including:

- chills
- body aches
- fever
- confusion

- nausea
- vomiting
- stomach pain
- weakness

- diarrhea
- cough or shortness of breath
- burning or pain when you urinate
- skin rash

See "What are the possible side effects of GAVRETO?" for more information about side effects.

What is GAVRETO?

GAVRETO is a prescription medicine used to treat certain cancers caused by abnormal rearranged during transfection (RET) genes in:

- adults with non-small cell lung cancer (NSCLC) that has spread.
- adults and children 12 years of age and older with advanced thyroid cancer or thyroid cancer that has spread who require a medicine by mouth or injection (systemic therapy) and who have received radioactive iodine and it did not work or is no longer working.

Your healthcare provider will perform a test to make sure that GAVRETO is right for you.

It is not known if GAVRETO is safe and effective when used to treat cancers caused by abnormal RET genes:

- in children for the treatment of NSCLC or
- in children younger than 12 years of age for the treatment of thyroid cancer.

Before taking GAVRETO, tell your healthcare provider about all of your medical conditions, including if you:

- have an infection. See "What is the most important information I should know about GAVRETO?"
- have lung or breathing problems other than lung cancer
- have high blood pressure
- have bleeding problems
- have liver problems
- plan to have surgery. You should stop taking GAVRETO at least 5 days before your planned surgery. See "What are the possible side effects of GAVRETO?"
- are pregnant or plan to become pregnant. GAVRETO can harm your unborn baby.
  Females who are able to become pregnant:
  - Your healthcare provider will do a pregnancy test before you start treatment with GAVRETO.
  - You should use an effective form of non-hormonal birth control (contraception) during treatment and for 2 weeks after your last dose of GAVRETO.
  - Birth control methods that contain hormones (such as birth control pills, injections or transdermal system patches) may not work as well during treatment with GAVRETO.
  - Talk to your healthcare provider about birth control methods that may be right for you during this time.
  - Tell your healthcare provider right away if you become pregnant or think you might be pregnant during treatment with GAVRETO.
  Males with female partners who are able to become pregnant:
  - You should use effective birth control (contraception) during treatment and for 1 week after your last dose of GAVRETO.
- are breastfeeding or plan to breastfeed. It is not known if GAVRETO passes into your breast milk. Do not breastfeed during treatment and for 1 week after your last dose of GAVRETO.

Tell your healthcare provider about all the medicines you take, including prescription and over-the-counter medicines, vitamins, and herbal supplements. Taking GAVRETO with other medicines may affect how GAVRETO works.

How should I take GAVRETO?

- Take GAVRETO exactly as your healthcare provider tells you to take it.
- Take your prescribed dose of GAVRETO 1 time each day.
- Take GAVRETO on an empty stomach. Do not eat for at least 2 hours before and at least 1 hour after taking GAVRETO.
- Do not change your dose or stop taking GAVRETO unless your healthcare provider tells you to.
- Your healthcare provider may change your dose, temporarily stop, or permanently stop treatment with GAVRETO if you develop side effects.
- If you miss a dose of GAVRETO, take it as soon as possible on the same day. Then take your next dose of GAVRETO at your regular time the next day.
- If you vomit after taking a dose of GAVRETO, do not take an extra dose. Take your next dose of GAVRETO at your regular time the next day.

What are the possible side effects of GAVRETO?

GAVRETO may cause serious side effects, including:

- See "What is the most important information I should know about GAVRETO?"
- Lung problems. GAVRETO may cause severe or life-threatening inflammation of the lungs during treatment, that can lead to death. Tell your healthcare provider right away if you have any new or worsening symptoms, including:

- shortness of breath

- cough

- fever

- High blood pressure (hypertension). High blood pressure is common with GAVRETO and may sometimes be severe. You should check your blood pressure regularly during treatment with GAVRETO. Tell your healthcare provider if you have increased blood pressure readings or get any symptoms of high blood pressure, including:

- confusion
- headaches
- shortness of breath

- dizziness
- chest pain

- Liver problems. Liver problems (increased liver function blood test results) can happen during treatment with GAVRETO and may sometimes be serious. Your healthcare provider will do blood tests before and during treatment with GAVRETO to check you for liver problems. Tell your healthcare provider right away if you get any signs or symptoms of liver problem during treatment, including:

- yellowing of your skin or the white part of your eyes (jaundice)
- dark "tea-colored" urine
- sleepiness
- bleeding or bruising

- loss of appetite
- nausea or vomiting
- pain on the upper right side of your stomach area

- Bleeding problems. GAVRETO can cause bleeding which can be serious and cause death. Tell your healthcare provider if you have any signs or symptoms of bleeding during treatment, including:

- vomiting blood or if your vomit looks like coffee grounds
- pink or brown urine
- red or black (looks like tar) stools
- coughing up blood or blood clots
- unusual bleeding or bruising of your skin
- menstrual bleeding that is heavier than normal

- unusual vaginal bleeding
- nose bleeds that happen often
- drowsiness or difficulty being awakened
- confusion
- headache
- change in speech

- Tumor lysis syndrome (TLS). TLS is caused by a fast breakdown of cancer cells. TLS can cause you to have kidney failure and the need for dialysis treatment, an abnormal heartbeat, and may sometimes lead to hospitalization. Your healthcare provider may do blood tests to check you for TLS. You should stay well hydrated during treatment with GAVRETO. Call your healthcare provider or get emergency medical help right away if you develop any of these symptoms during treatment with GAVRETO:

- nausea
- vomiting
- weakness
- swelling

- shortness of breath
- muscle cramps
- seizures

- Risk of wound healing problems. Wounds may not heal properly during treatment with GAVRETO. Tell your healthcare provider if you plan to have any surgery before or during treatment with GAVRETO.
  - You should not take GAVRETO for at least 5 days before surgery.
  - Your healthcare provider should tell you when you may start taking GAVRETO again after surgery.

The most common side effects of GAVRETO include:

- muscle and joint pain
- constipation
- diarrhea
- tiredness

- swelling of your face, arms, legs, hands, and feet (edema)
- fever
- cough

The most common severe abnormal blood test results with GAVRETO include:

- decreased white blood cell, red blood cell, and platelet counts
- decreased levels of phosphate, body salt (sodium), calcium and potassium in the blood
- abnormal liver function blood tests
- increased levels of enzyme called alkaline phosphatase in the blood (test for liver or bone problems)
- increased levels of potassium in the blood

GAVRETO may affect fertility in males and females, which may affect your ability to have children. Talk to your healthcare provider if this is a concern for you.

These are not all the possible side effects of GAVRETO.

Call your doctor for medical advice about side effects. You may report side effects to FDA at 1-800-FDA-1088.

How should I store GAVRETO?

- Store GAVRETO at room temperature between 68°F to 77°F (20°C to 25°C).
- Protect GAVRETO from moisture.

Keep GAVRETO and all medicines out of the reach of children.

General information about the safe and effective use of GAVRETO.

Medicines are sometimes prescribed for purposes other than those listed in a Patient Information leaflet. Do not use GAVRETO for a condition for which it was not prescribed. Do not give GAVRETO to other people, even if they have the same symptoms that you have. It may harm them. You can ask your pharmacist or healthcare provider for information about GAVRETO that is written for health professionals.

What are the ingredients in GAVRETO?

Active ingredient: pralsetinib

Inactive ingredients: citric acid, hydroxypropyl methylcellulose (HPMC), magnesium stearate, microcrystalline cellulose (MCC), pregelatinized starch and sodium bicarbonate.

Capsule shell: FD&C Blue #1 (Brilliant Blue FCF), hypromellose and titanium dioxide.

White printing ink: butyl alcohol, dehydrated alcohol, isopropyl alcohol, potassium hydroxide, propylene glycol, purified water, shellac, strong ammonia solution and titanium dioxide.

Manufactured for: Rigel Pharmaceuticals, Inc., South San Francisco, CA 94080
GAVRETO® is a registered trademark of Rigel Pharmaceuticals, Inc.
For more information, go to www.GAVRETO.com or call 1-800-983-1329.

This Medication Guide has been approved by the U.S. Food and Drug Administration.

Revised: 12/2025

PRINCIPAL DISPLAY PANEL - 60 Capsule - Carton

NDC 71332-006-60

GAVRETO®
(pralsetinib)
capsules

100 mg

For Oral Use

Rx only

60 Capsules

rigel®

PRINCIPAL DISPLAY PANEL - 90 Capsule - Carton

NDC 71332-006-90

GAVRETO®
(pralsetinib)
capsules

100 mg

For Oral Use

Rx only

90 Capsules

rigel®